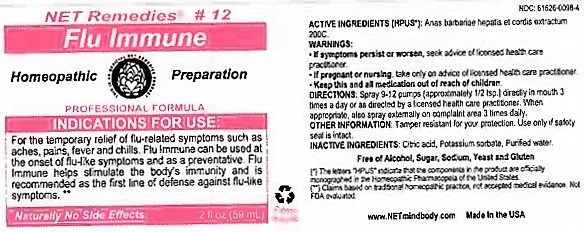 DRUG LABEL: Flu Immune
NDC: 61626-0098 | Form: LIQUID
Manufacturer: NET Remedies
Category: homeopathic | Type: HUMAN PRESCRIPTION DRUG LABEL
Date: 20210119

ACTIVE INGREDIENTS: CAIRINA MOSCHATA HEART/LIVER AUTOLYSATE 200 [hp_C]/59 mL
INACTIVE INGREDIENTS: CITRIC ACID MONOHYDRATE; POTASSIUM SORBATE; WATER

Flu Immune

ACTIVE INGREDIENT

ACTIVE INGREDIENTS (HPUS*): Anas barbariae hepatis et cordis extractum 200C.

(*) The letters "HPUS" indicate that the components in the product are officially monographed in the Homeopathic Pharmacopeia of the United States.

(**) Claims based on traditional homeopathic practice, not accepted medical evidence. Not FDA evaluated.

INDICATIONS AND USAGE

INDICATIONS FOR USE: For the temporary relief of flu-related symptoms such as aches, pains, fever and chills. Flu Immune can be used at the onset of flu-like symptoms and as preventative. Flu Immune helps stimulate the body's immunity and is reccommended as first line of defense against flu-like symptoms. **

WARNINGS

WARNINGS:• If symptoms persist or worsen, seek advice of licensed health care practitioner.

• If pregnant or nursing, take on only advice of licensed heatlh care practitioner.

• Keep this and all medications out of reach of children.

KEEP OUT OF REACH OF CHILDREN

• Keep this and all medications out of reach of children.

DOSAGE AND ADMINISTRATION

DIRECTIONS: Spray 9-12 pumps (approximately 1/2 tsp.) directly in mouth 3 times a day or as directed by licensed health care practitioner. When appropriate, also spray externally on complaint area 3 times daily.

OTHER INFORMATION: Tamper resistant for your protection. Use only if safety seal is intact.

INACTIVE INGREDIENTS: Citrid acid, Potassium sorbate, Purified water.

Free of Alcohol, Sugar, Sodium, Yeast and Gluten.

QUESTIONS

www.NETmindbody.com

Made in the USA.

PACKAGE LABEL

NET Remedies #12

Flu Immune

Homeopathic Preparation

PROFESSIONAL FORMULA

Naturally No Side Effects

2 fl oz (59 mL)

PURPOSE

INDICATIONS FOR USE: For the temporary relief of flu-related symptoms such as aches, pains, fever and chills. Flu Immune can be used at the onset of flu-like symptoms and as preventative. Flu Immune helps stimulate the body's immunity and is reccommended as first line of defense against flu-like symptoms. **